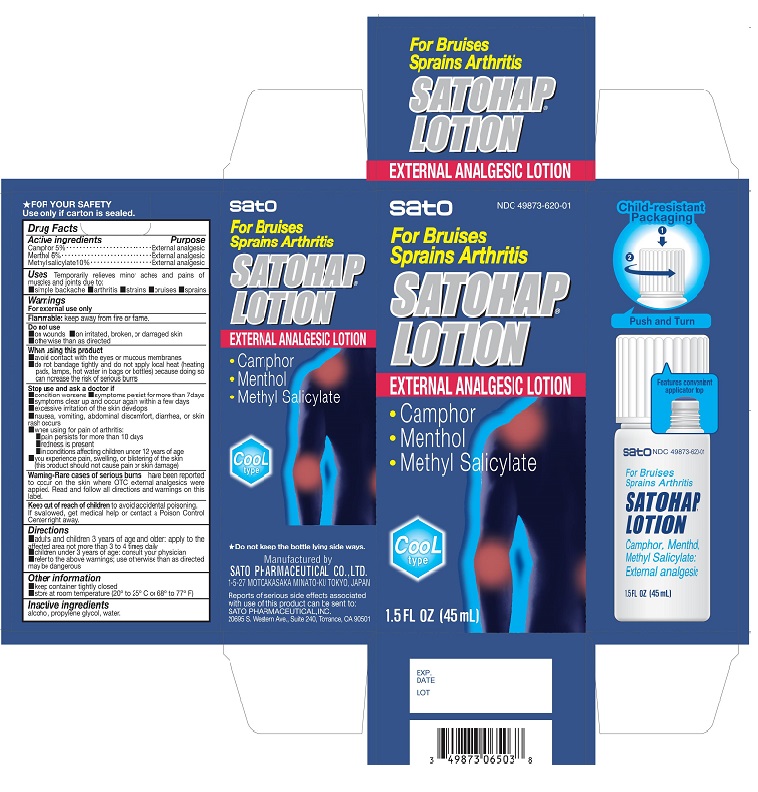 DRUG LABEL: Satohap Cool Type
NDC: 49873-620 | Form: LOTION
Manufacturer: Sato Pharmaceutical Co., Ltd.
Category: otc | Type: HUMAN OTC DRUG LABEL
Date: 20231107

ACTIVE INGREDIENTS: CAMPHOR (SYNTHETIC) 5 g/100 mL; LEVOMENTHOL 6 g/100 mL; METHYL SALICYLATE 10 g/100 mL
INACTIVE INGREDIENTS: ALCOHOL; PROPYLENE GLYCOL; WATER

Satohap Lotion (Cool Type)

Active ingredients

Camphor

Menthol

Methyl salicylate

Purpose

Camphor External analgesic

Menthol External analgesic

Methyl salicylate External analgesic

INDICATIONS AND USAGE

Uses Temporarily relieves minor aches and pains of muscles and joints due to:

- simple backache
- arthritis
- strains
- bruises
- sprains

Warnings

For external use only

Flammable: Keep away from fire or flame

Do not use

- on wounds
- on irritated, broken, or damaged skin
- otherwise than as directed

When using this product

- avoid contact with the eyes or mucous membranes
- do not bandage tightly and do not apply local heat (heating pads, lamps, hot water in bags or bottles) because doing so can increase the risk of serious burns

Stop use and ask a doctor if

- condition worsens
- symptoms persist for more than 7 days
- symptoms clear up and occur again within a few days
- excessive irritation of the skin develops
- nausea, vomiting, abdominal discomfort, diarrhea, or skin rash occurs
- when using for pain of arthritis:
- pain persists for more than 10 days
- redness is present
- in conditions affecting children under 12 years of age
- you experience pain, swelling, or blistering of the skin (this product should not cause pain or skin damage)

USER SAFETY WARNINGS

Warning-Rare cases of serious burns have been reported to occur on the skin where OTC external analgesics were applied. Read and follow all directions and warnings on this label.

Keep out of reach of children to avoid accidental poisoning. If swallowed, get medical help or contact a Poison Control Center right away.

Directions

- adults and children 3 years of age and older: apply to the affected area not more than 3 to 4 times daily
- children under 3 years of age: consult your physician
- refer to the above warnings; use otherwise than as directed may be dangersous

Other information

- keep container tightly closed
- store at room temperature (20° to 25° C or 68° to 77° F)

Inactive ingredients

alcohol, propylene glycol, water.